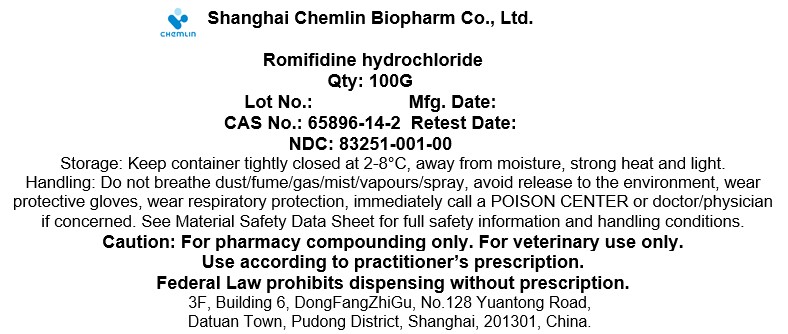 DRUG LABEL: Romifidine hydrochloride
NDC: 83251-001 | Form: POWDER
Manufacturer: Shanghai Chemlin Biopharm Co., Ltd.
Category: other | Type: BULK INGREDIENT - ANIMAL DRUG
Date: 20241003

ACTIVE INGREDIENTS: Romifidine hydrochloride 1 g/1 g

Romifidine hydrochloride